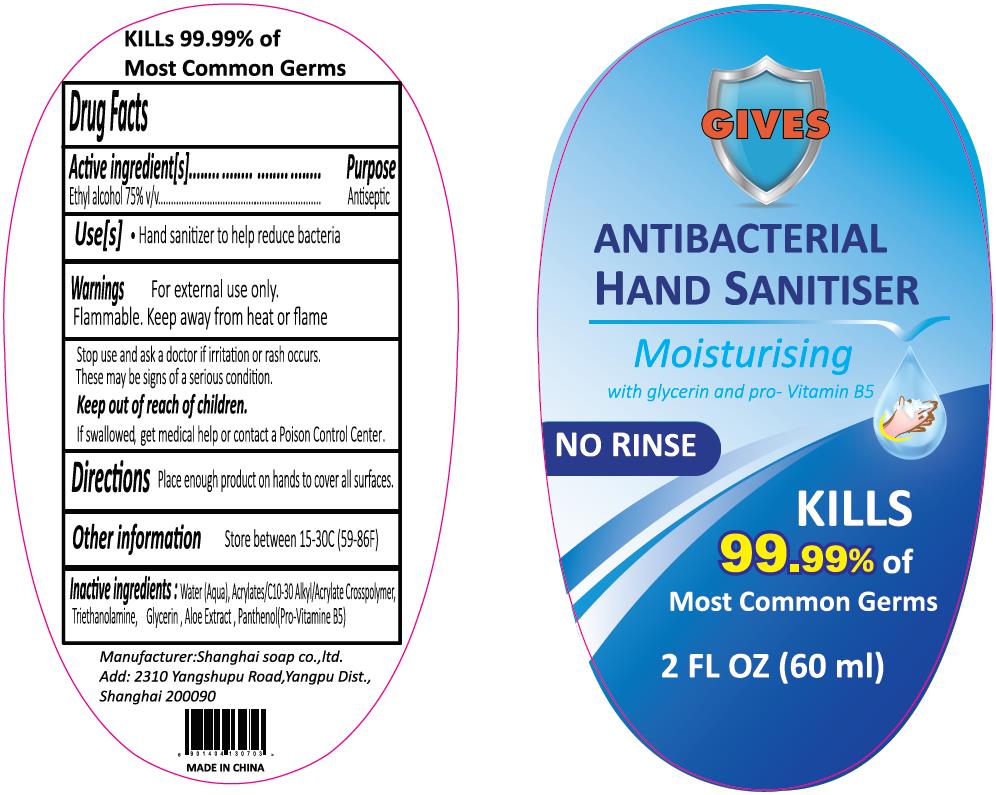 DRUG LABEL: HAND SANITIZER
NDC: 76390-0101 | Form: GEL
Manufacturer: Shanghai Soap Co., Ltd.
Category: otc | Type: HUMAN OTC DRUG LABEL
Date: 20200611

ACTIVE INGREDIENTS: ALCOHOL 45 mL/60 mL
INACTIVE INGREDIENTS: GLYCERIN; WATER; CARBOMER INTERPOLYMER TYPE A (ALLYL SUCROSE CROSSLINKED); TROLAMINE; DEXPANTHENOL; ALOE

SSC, Sanitizer, 75% Alcohol, Gel; 060mL

Active Ingredient(s)

Ethyl alcohol 75% v/v. Purpose: Antiseptic

Purpose

Antiseptic

Use

Hand sanitizer to help reduce bacteria.

Warnings

For external use only.

Flammable. Keep away from heat or flame.

Do not use in or near the eyes.

When using this product do not use in or near the eyes.

If case of contact, rinse eyes thoroughly with water.

Stop use and ask a doctor if irritation or rash occurs.

Thess may be signs of a serious condition.

Keep out of reach of children.

If swallowed, get medical help or contact a Poison Control Center.

Directions

Place enough product on hands to cover all surfaces.

Other information

Store between 15-30℃ (59-86℉).

Inactive ingredients

Water (Aqua), Acrylates/C10-30 Alkyl/Acrylate Crosspolymer, Triethanolamine, Glycerin, Aloe Extract, Panthenol (pro-Vitamin B5)